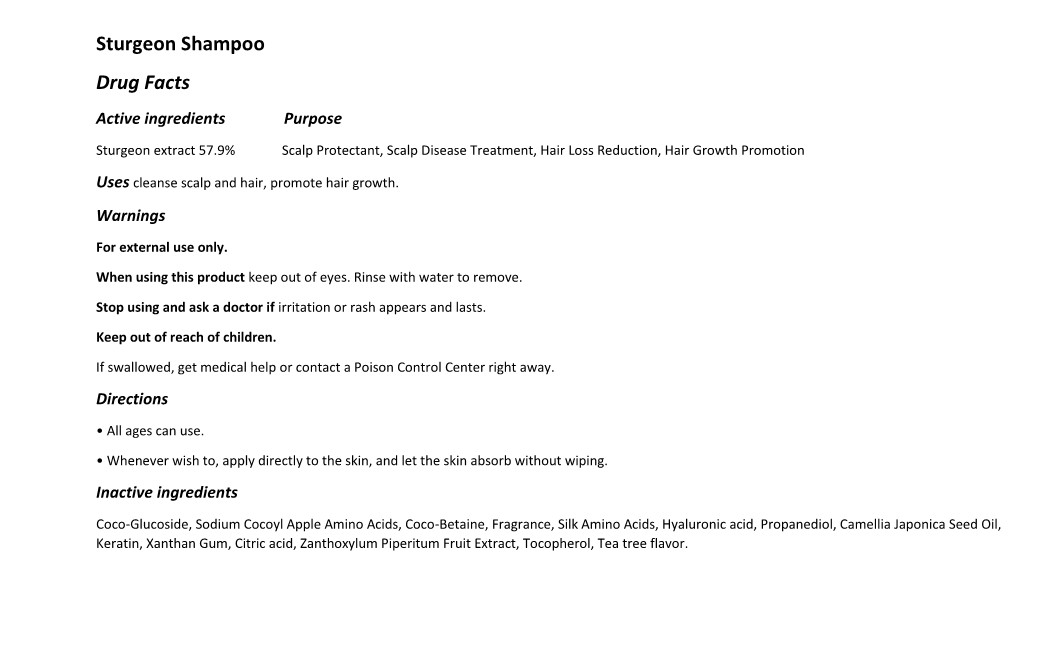 DRUG LABEL: The Zoeun Skin Total Care-Shampoo
NDC: 83636-501 | Form: SHAMPOO
Manufacturer: Sturgeonbio Co.,Ltd.
Category: otc | Type: HUMAN OTC DRUG LABEL
Date: 20250120

ACTIVE INGREDIENTS: STURGEON, UNSPECIFIED 57.9 g/100 mL
INACTIVE INGREDIENTS: TEA LEAF OIL; XANTHAN GUM; TOCOPHEROL; CITRIC ACID MONOHYDRATE; BUTYLENE GLYCOL; ZANTHOXYLUM PIPERITUM FRUIT PULP; MELALEUCA ALTERNIFOLIA (TEA TREE) LEAF OIL; PROPANEDIOL; SODIUM COCOYL APPLE AMINO ACIDS; COCO GLUCOSIDE; FRAGRANCE CLEAN ORC0600327; COCAMIDOPROPYL BETAINE; CAPRYLYL/CAPRYL OLIGOGLUCOSIDE; COCODIMONIUM HYDROXYPROPYL HYDROLYZED KERATIN (1000 MW)

83636-501 The Zoeun Skin Total Care Shampoo

Active Ingredients

Sturgeon extract 57.9%

Purpose

Scalp Protectant, Scalp Disease Treatment, Hair Loss Reduction, Hair Growth Promotion

Uses

cleanse scalp and hair, promote hair growth

Warnings

Keep out of reach of children.
If swallowed, get medical help or contact a Poison Control Center right away.

Warnings

Stop using and ask a doctor if irritation or rash appears and lasts.

Warnings

When using this product keep out of eyes. Rinse with water to remove.

Warnings

For external use only.

Directions

• All ages can use.
• Whenever wish to, apply directly to the skin, and let the skin absorb without wiping.

Inactive Indgredients

Coco-Glucoside, Sodium Cocoyl Apple Amino Acids, Coco-Betaine, Fragrance, Silk Amino Acids, Hyaluronic acid, Propanediol, Camellia Japonica Seed Oil,
Keratin, Xanthan Gum, Citric acid, Zanthoxylum Piperitum Fruit Extract, Tocopherol, Tea tree flavor.